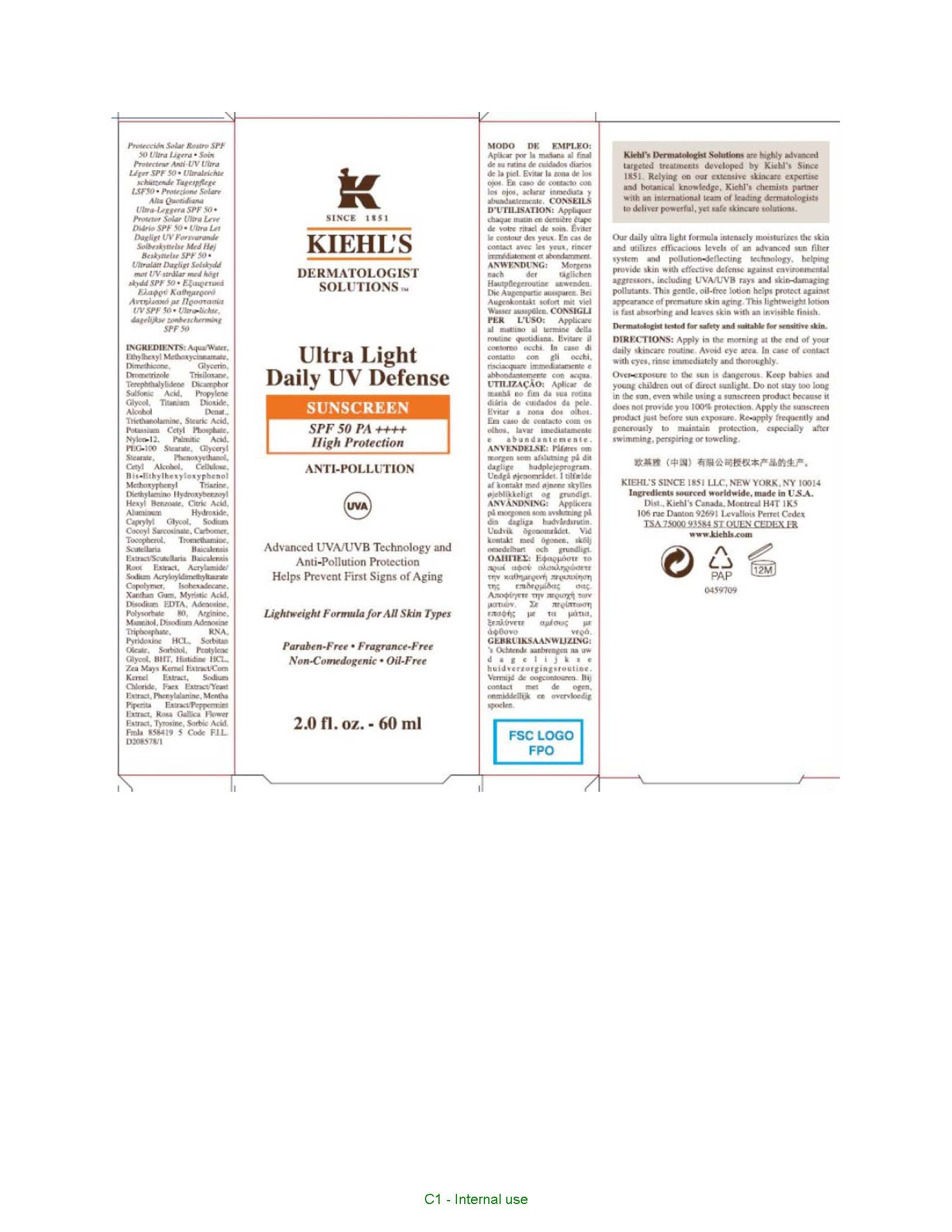 DRUG LABEL: KIEHLS DERMATOLOGIST SOLUTIONS ULTRA LIGHT DAILY UV DEFENSE SUNSCREEN SPF 50 HIGH PROTECTION ANTI-POLLUTION LIGHTWEIGHT FORMULA FOR ALL SKIN TYPES
NDC: 49967-449 | Form: LOTION
Manufacturer: L'Oreal USA Products, Inc.
Category: otc | Type: HUMAN OTC DRUG LABEL
Date: 20260107

ACTIVE INGREDIENTS: DROMETRIZOLE TRISILOXANE 40 mg/1 mL; TITANIUM DIOXIDE 40 mg/1 mL; ECAMSULE 120 mg/1 mL; BEMOTRIZINOL 5 mg/1 mL; DIETHYLAMINO HYDROXYBENZOYL HEXYL BENZOATE 5 mg/1 mL; OCTINOXATE 67.5 mg/1 mL
INACTIVE INGREDIENTS: WATER; DIMETHICONE; GLYCERIN; PROPYLENE GLYCOL; ALCOHOL; TROLAMINE; STEARIC ACID; POTASSIUM CETYL PHOSPHATE; NYLON-12; PALMITIC ACID; PEG-100 STEARATE; GLYCERYL MONOSTEARATE; PHENOXYETHANOL; CETYL ALCOHOL; POWDERED CELLULOSE; CITRIC ACID MONOHYDRATE; ALUMINUM HYDROXIDE; CAPRYLYL GLYCOL; SODIUM COCOYL SARCOSINATE; CARBOXYPOLYMETHYLENE; TOCOPHEROL; TROMETHAMINE; SCUTELLARIA BAICALENSIS ROOT; ISOHEXADECANE; XANTHAN GUM; MYRISTIC ACID; EDETATE DISODIUM; ADENOSINE; POLYSORBATE 80; ARGININE; MANNITOL; ADENOSINE TRIPHOSPHATE DISODIUM; PYRIDOXINE HYDROCHLORIDE; SORBITAN MONOOLEATE; SORBITOL; PENTYLENE GLYCOL; BUTYLATED HYDROXYTOLUENE; HISTIDINE MONOHYDROCHLORIDE; CORN; SODIUM CHLORIDE; YEAST, UNSPECIFIED; PHENYLALANINE; MENTHA PIPERITA; ROSA GALLICA FLOWER; TYROSINE; SORBIC ACID

Drug Facts

Ingredients

Drometrizole Trisiloxane

Titanium Dioxide

Terephthalylidene Dicamphor Sulfonic Acid

Bis-Ethylhexyloxyphenol Methoxyphenyl Triazine

Diethylamino Hydroxybenzoyl Hexyl Benzoate

Ethylhexyl Methoxycinnamate

Inactive ingredients

-Aqua/Water, Glycerin, Propylene Glycol, Alcohol Denat., Triethanolamine, Stearic Acid, Potassium Cetyl Phosphate, Nylon-12, Palmitic Acid, PEG-100 Stearate, Glyceryl Stearate, Phenoxyethanol, Cetyl Alcohol, Cellulose, Citric Acid, Aluminum Hydroxide, Caprylyl Glycol, Sodium Cocoyl Sarcosinate, Carbomer, Tocopherol, Tromethanime, Scutellaria Baicalensis Extract/Scutellaria Baicalensis Root Extract, Acrylamide/Sodium Acryloyldimethyltaurate Copolymer, Isohexadecane, Xanthan Gum, Myristic Acid, Disodium EDTA, Adenosine, Polysorbate 80, Arginine, Mannitol, Disodium Adenosine Triphosphate, RNA, Pyridoxane HCL, Sorbitan Oleate, Sorbitol, Pentylene Glycol, BHT, Histidine HCL, Zea Mays Kernel Extract/Corn Kernel Extract, Sodium Chloride, Faex Extract/Yeast Extract, Phenylalanine, Mentha Piperita Extract/Perppermint Extract, Rosa Gallica Flower Extract, Tyrosine, Sorbic Acid

Directions

Apply in the morning at the end of your daily skincare routine. Avoid eye area. In case of contact with eyes, rinse immediately and thoroughly.